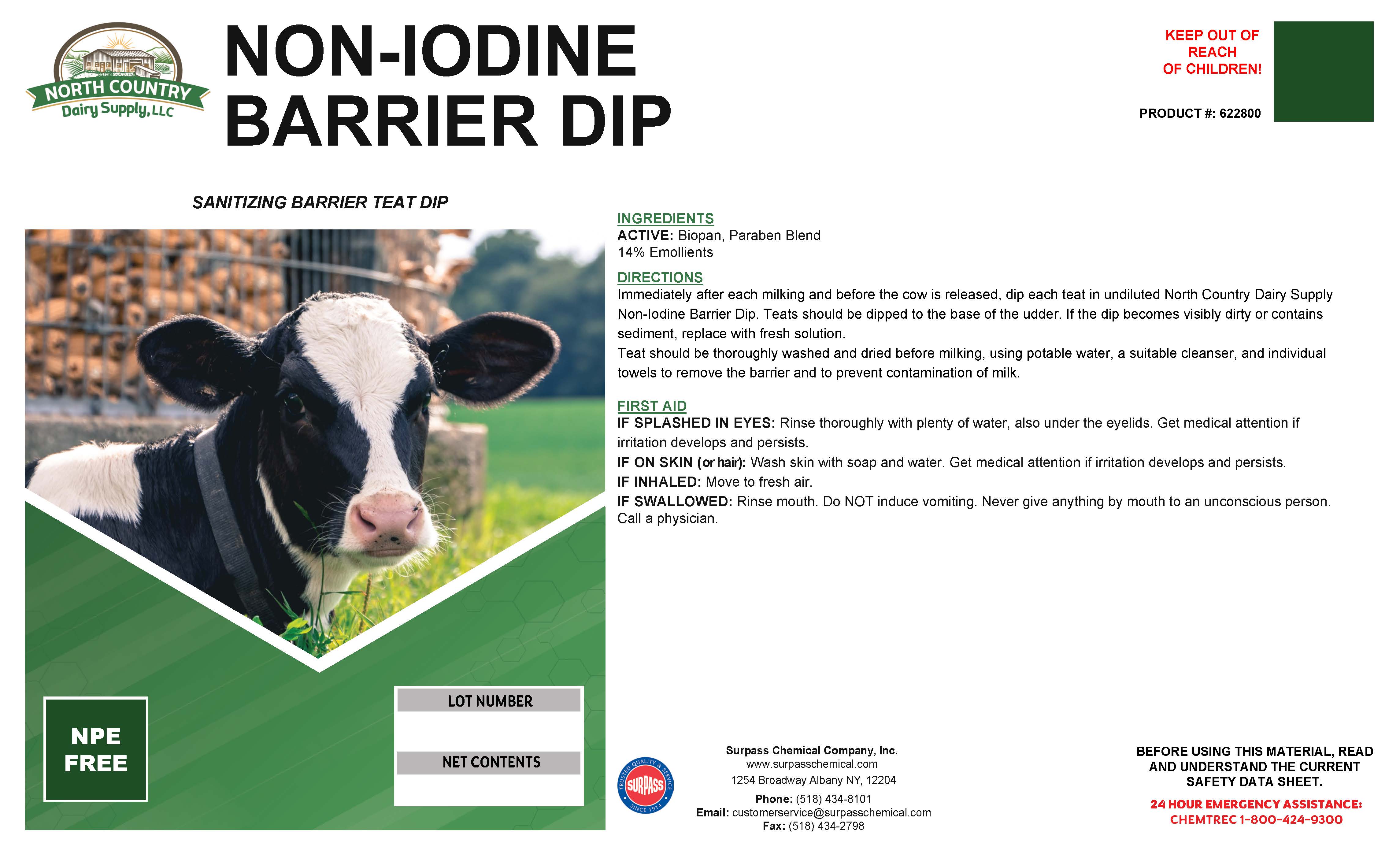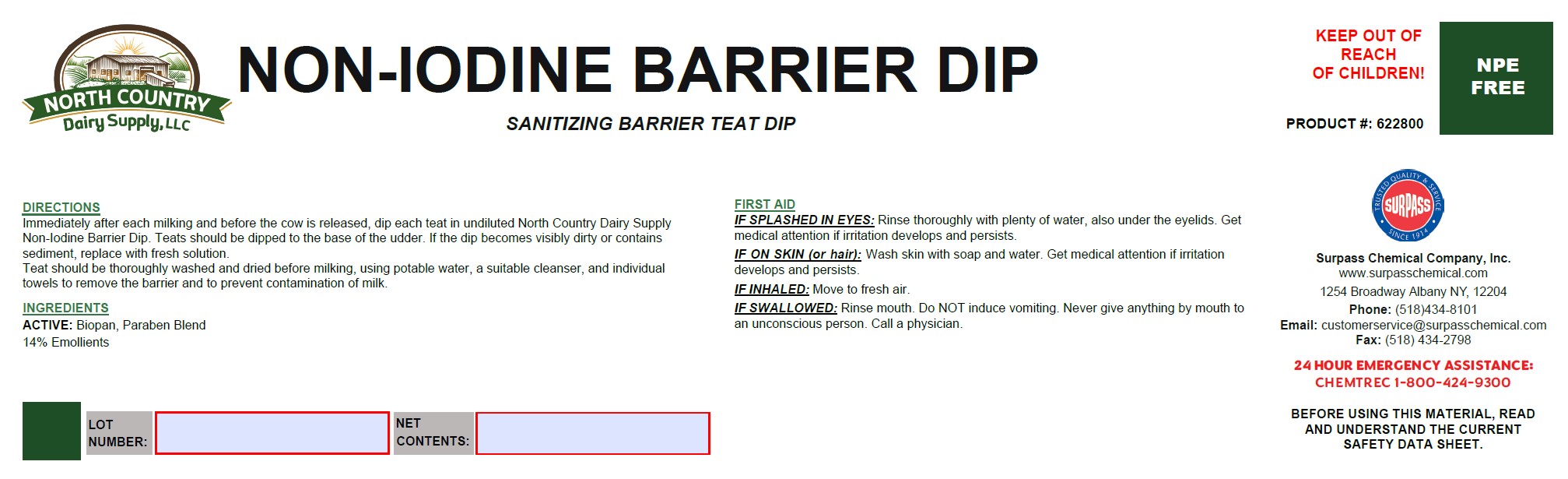 DRUG LABEL: Non Iodine Barrier Dip
NDC: 86067-0119 | Form: SOLUTION
Manufacturer: Surpass Chemical Company, Inc.
Category: animal | Type: OTC ANIMAL DRUG LABEL
Date: 20251229

ACTIVE INGREDIENTS: PROPYLPARABEN 0.001 kg/1 kg; METHYLPARABEN 0.001 kg/1 kg; PROPANEDIOL 0.002 kg/1 kg
INACTIVE INGREDIENTS: WATER 0.81182 kg/1 kg; C9-11 PARETH-3 0.01 kg/1 kg; LANOLIN 0.0889 kg/1 kg; PROPYLENE GLYCOL 0.01 kg/1 kg; GLYCERIN 0.05 kg/1 kg; FD&C YELLOW NO. 6 0.00013 kg/1 kg; FD&C YELLOW NO. 5 0.00011 kg/1 kg; ANHYDROUS CITRIC ACID 0.00004 kg/1 kg; XANTHAN GUM 0.005 kg/1 kg; BUTYLENE GLYCOL 0.01 kg/1 kg; 2-PROPANOL, 1,1'-OXYBIS(3-(1-NAPHTHALENYLOXY)- 0.01 kg/1 kg

Non Iodine Barrier Dip

DESCRIPTION

NON IODINE BARRIER DIP

SANITIZING BARRIER TEAT DIP PRODUCT #: 622800

DIRECTIONS:
Immediately after each milking and before the cow is released, dip each teat in undiluted North Country Dairy Supply Non-Iodine Barrier Dip. Teats should be dipped to the base of the udder. If the dip becomes visibly dirty or contains sediment, replace with fresh solution.

Teat should be thoroughly washed and dried before milking, using potable water, a suitable cleanser, and individualtowels to remove the barrier and to prevent contamination of milk.

ACTIVE INGREDIENT

INGREDIENTS:
ACTIVE: Biopan, Paraben Blend

14% Emolients

OTHER SAFETY INFORMATION

FIRST AID:
IF SPLASHED IN EYES: Rinse thoroughly with plenty of water, also under the eyelids. Get medical attention if irritation develops and persists.
IF ON SKIN (or hair): Wash skin with soap and water. Get medical attention if irritation develops and persists.
IF INHALED: Remove to fresh air.
IF SWALLOWED: Rinse mouth. Do NOT induce vomiting. Never give anything by mouth to an unconscious person. Call a physician.

USER SAFETY WARNINGS

BEFORE USING THIS MATERIAL, READ AND
UNDERSTAND THE CURRENT SAFETY DATA SHEET.

Surpass Chemical Company, Inc. Phone: (518) 434-8101 24 HOUR EMERGENCY ASSISTANCE:
www.surpasschemical.com Fax: (518) 434-2798 CHEMTREC 1-800-424-9300
1254 Broadway Albany NY, 12204 Email: customerservice@surpasschemical.com

KEEP OUT OF REACH OF CHILDREN!